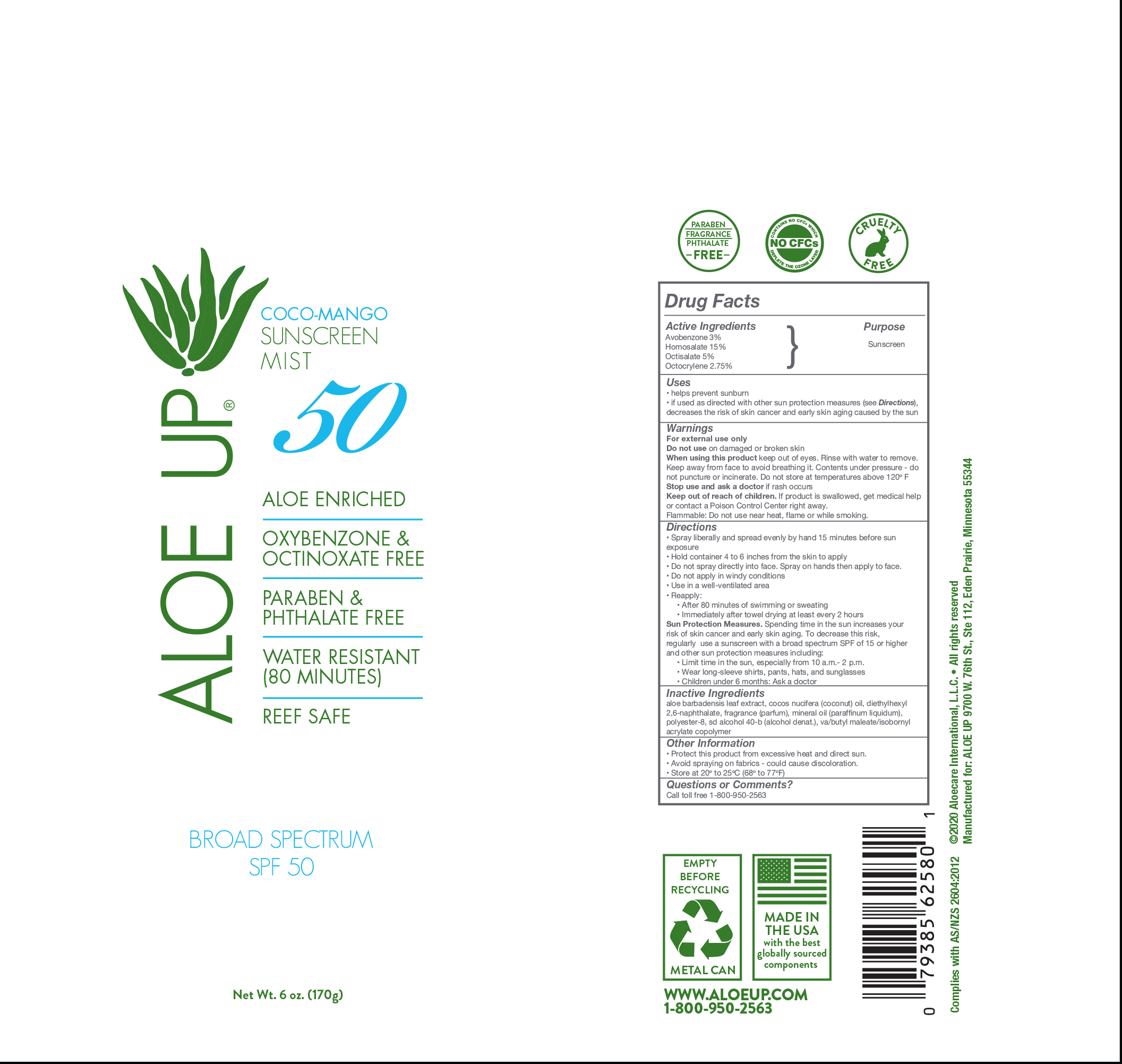 DRUG LABEL: Aloe Up SPF 50 Coco-Mango C-spray
NDC: 73440-2580 | Form: AEROSOL, SPRAY
Manufacturer: Cross Brands Contract Filling
Category: otc | Type: HUMAN OTC DRUG LABEL
Date: 20210219

ACTIVE INGREDIENTS: AVOBENZONE 5.1 g/170 g; OCTISALATE 8.5 g/170 g; HOMOSALATE 25.5 g/170 g; OCTOCRYLENE 4.7 g/170 g
INACTIVE INGREDIENTS: ALCOHOL 104 g/170 g

Aloe Up SPF 50 Coco-Mango C-spray